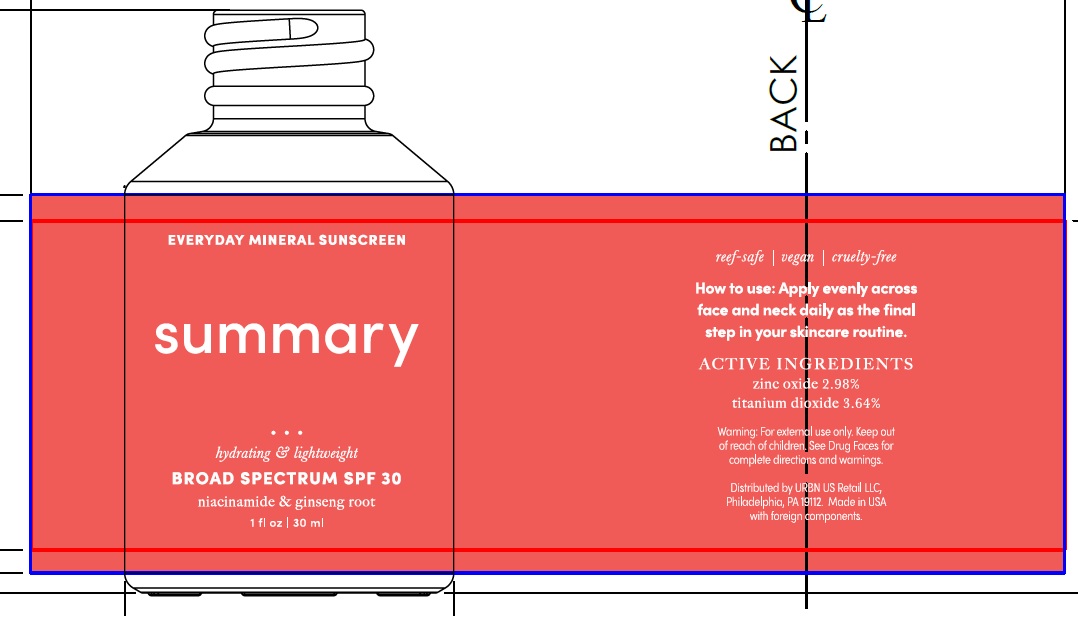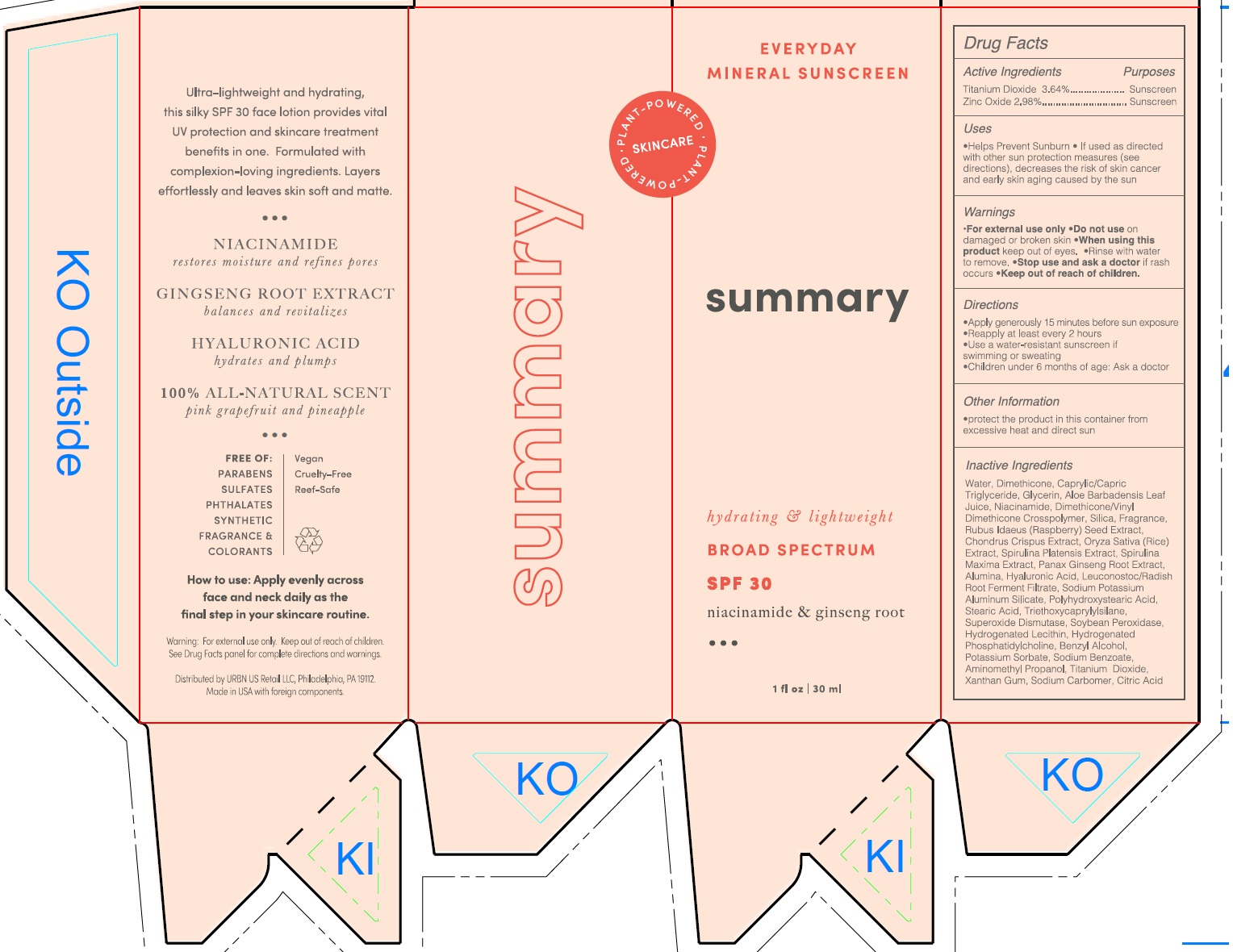 DRUG LABEL: SUMMARY EVERYDAY MINERAL SUNSCREEN BROAD SPECTRUM SPF 30
NDC: 14268-120 | Form: LOTION
Manufacturer: ENGLEWOOD LAB, INC.
Category: otc | Type: HUMAN OTC DRUG LABEL
Date: 20231212

ACTIVE INGREDIENTS: TITANIUM DIOXIDE 364 mg/1 mL; ZINC OXIDE 298 mg/1 mL
INACTIVE INGREDIENTS: WATER; DIMETHICONE; MEDIUM-CHAIN TRIGLYCERIDES; GLYCERIN; ALOE VERA LEAF; NIACINAMIDE; SILICON DIOXIDE; RUBUS IDAEUS SEED; CHONDRUS CRISPUS CARRAGEENAN; RICE GERM; ARTHROSPIRA MAXIMA; ASIAN GINSENG; ALUMINUM OXIDE; HYALURONIC ACID; LEUCONOSTOC/RADISH ROOT FERMENT FILTRATE; STEARIC ACID; TRIETHOXYCAPRYLYLSILANE; SUPEROXIDE DISMUTASE (SACCHAROMYCES CEREVISIAE); BENZYL ALCOHOL; POTASSIUM SORBATE; SODIUM BENZOATE; AMINOMETHYLPROPANOL; XANTHAN GUM; CITRIC ACID MONOHYDRATE

SUMMARY EVERYDAY MINERAL SUNSCREEN BROAD SPECTRUM SPF 30

Active Ingredients

Titanium Dioxide 3.64%

Zinc Oxide 2.98%

Purposes

Sunscreen

Uses

- Helps Prevent Sunburn
- If used as directed with other sun protection measures (see directions), decreases the risk of skin cancer and early skin aging caused by the sun

Warnings

- For external use only

Do not use

- on damaged or broken skin

When using this product

- keep out of eyes.
- Rinse with water to remove.

Stop use and ask a doctor

ir rash occurs

Directions

- Apply generously 15 minutes before sun exposure
- Reapply at least every 2 hours
- Use a water-resistant sunscreen if swimming or sweating
- Children under 6 months of age: Ask a doctor

Other Information

- protect the product in this container from excessive heat and direct sun

Inactive Ingredients

Water, Diemthicone, Caprylic/Capric Triglyceride, Glycerin, Aloe Barbadensis Leaf Juice, Niacinamide, Dimethicone/Vinyl Dimethicone Crosspolymer, Silica, Fragrance, Rubus Idaeus(Raspberry) Seed Extract, Chondrus Crispus Extract, Oryza Sativa (Rice) Extract, Spirulina Platensis Extract, Spirulina Maxima Extract, Panax Ginseng Root Extract, Alumina, Hyaluronic Acid, Leuconostoc/Radish Root Ferment Filtrate, Sodium Potassium Aluminum Silicate, Polyhydroxystearic Acid, Stearic Acid, Triethoxycaprylylsilane, Superoxide Dismutase, Soybean Peroxidase, Hydrogenated Lecithin, Hydrogenated Phosphatidylcholine, Benzyl Alcohol, Potassium Sorbate, Sodium Benzoate, Aminomethyl Propanol, Titanium Dioxide, Xanthan Gum, Sodium Carbomer, Citric Acid